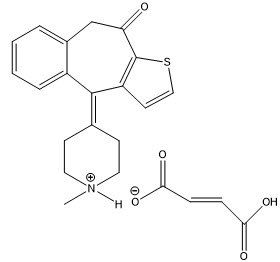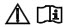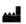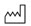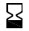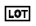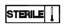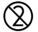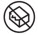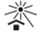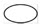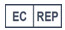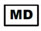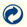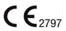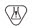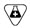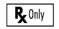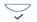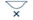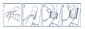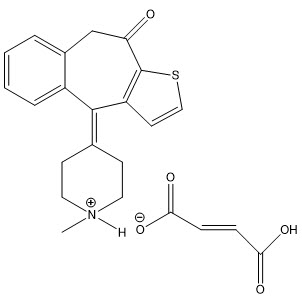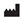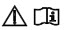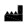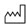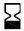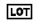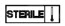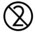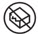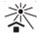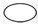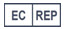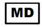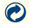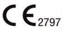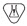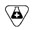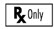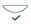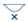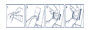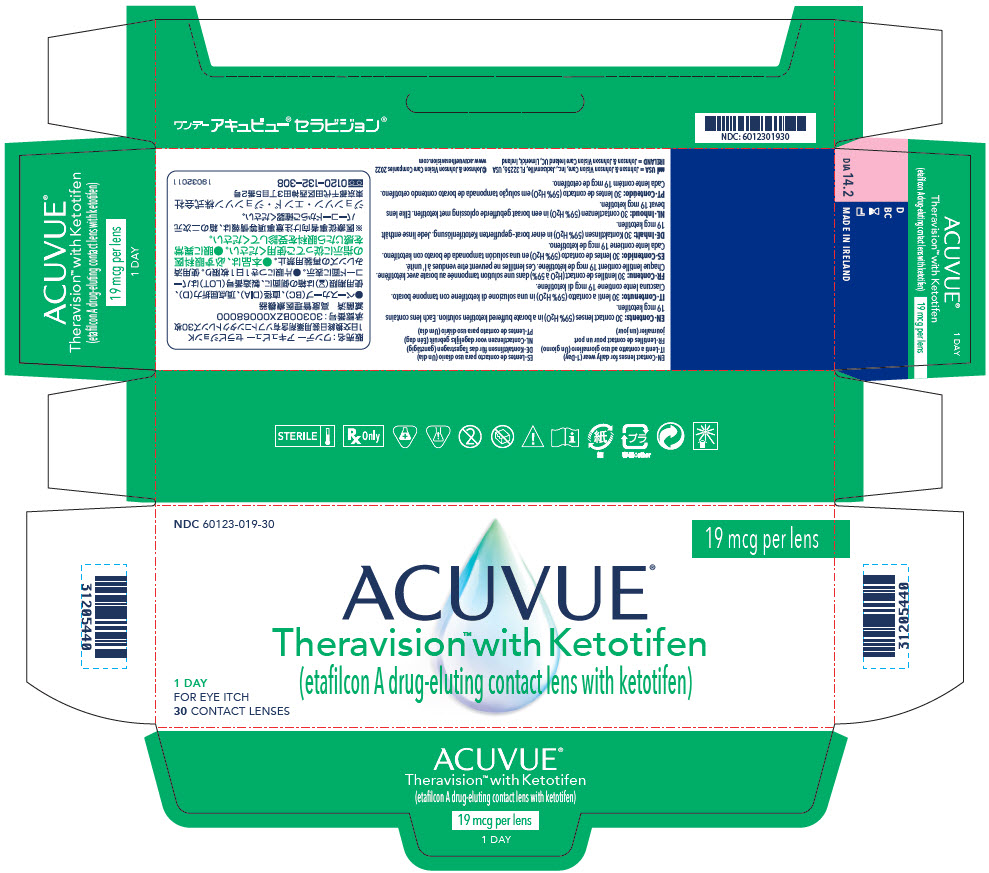 DRUG LABEL: ACUVUE Theravision with Ketotifen
NDC: 60123-019 | Form: drug-eluting contact lens
Manufacturer: Johnson & Johnson Vision Care, Inc.
Category: prescription | Type: HUMAN PRESCRIPTION DRUG LABEL
Date: 20220311

ACTIVE INGREDIENTS: ketotifen fumarate 0.019 mg/1 1
INACTIVE INGREDIENTS: WATER; PENTETIC ACID; SODIUM CHLORIDE; BORIC ACID; SODIUM BORATE

HIGHLIGHTS OF PRESCRIBING INFORMATION

These highlights do not include all the information needed to use ACUVUE® THERAVISION™ WITH KETOTIFEN safely and effectively. See full prescribing information for ACUVUE® THERAVISION™ WITH KETOTIFEN.
ACUVUE® THERAVISION™ WITH KETOTIFEN (etafilcon A drug-eluting contact lens with ketotifen), for ophthalmic use
Initial U.S. Approval: 2022

1 INDICATIONS AND USAGE

ACUVUE® Theravision™ with Ketotifen is a daily wear, daily disposable etafilcon A drug-eluting contact lens packaged with an H1 histamine receptor antagonist, indicated for the prevention ocular itch due to allergic conjunctivitis and correction of refractive ametropia (myopia and hyperopia) in aphakic and/or phakic patients who do not have red eye(s), are suitable for contact lens wear and do not have more than 1 D of astigmatism. (1)

2 DOSAGE AND ADMINISTRATION

- Insert one lens per eye per day. Discard lens after a single day's use. (2.1)
- Lenses should be removed prior to sleeping. (2.1)

3 DOSAGE FORMS AND STRENGTHS

Daily disposable etafilcon A drug-eluting contact lens with ketotifen (19 mcg per lens) (3)

4 CONTRAINDICATIONS

- Ocular Hyperemia (4.1)
- Corneal Hypoesthesia (4.2)
- Corneal Infections (4.3)

5 WARNINGS AND PRECAUTIONS

- Corneal Ulcer: Remove lenses (5.1)
- Contact Lens Related Complications: Remove lenses (5.2)
- Chemical Exposures: Flush eyes with water (5.3)
- Acanthamoeba Keratitis: Do not wear while swimming (5.4)

6 ADVERSE REACTIONS

The most commonly observed adverse reactions in clinical studies, occurring in ≥ 1% of ACUVUE® Theravision™ with Ketotifen treated eyes, were eye irritation, eye pain, and instillation site pain. (6.1)

To report SUSPECTED ADVERSE REACTIONS, contact Johnson & Johnson Vision Care, Inc. at 1-800-843-2020 or FDA at 1-800-FDA-1088 or www.fda.gov/medwatch.

FULL PRESCRIBING INFORMATION

1 INDICATIONS AND USAGE

ACUVUE® Theravision™ with Ketotifen is a daily wear, daily disposable etafilcon A drug-eluting contact lens for prevention ocular itch due to allergic conjunctivitis and correction of refractive ametropia (myopia and hyperopia) in aphakic and/or phakic patients who do not have red eye(s), are suitable for contact lens wear and do not have more than 1 D of astigmatism.

The lens contains an H1 histamine receptor antagonist for the prevention of ocular itch due to allergic conjunctivitis. The prevention of itch has been demonstrated to last through 12 hours in clinical trials; however, the lens may be worn for longer than 12 hours in a single day.

2 DOSAGE AND ADMINISTRATION

2.1 General Dosing Information

One ACUVUE® Theravision™ with Ketotifen should be inserted per eye per day. Discard lens after a single day's use. ACUVUE® Theravision™ with Ketotifen may be worn beyond twelve hours for vision correction. Lenses should be removed prior to sleeping.

The maximum daily wearing time should be determined by the Eye Care Professional based upon the patient's individual response to contact lenses. Patients tend to over wear the lenses initially. The Eye Care Professional should emphasize the importance of adhering to the initial maximum daily wearing time. Regular checkups, as determined by the Eye Care Professional, are also extremely important.

Eye drops containing benzalkonium chloride should not be used simultaneously with this product. Patients should wait 10 minutes after applying eye drop with benzalkonium chloride before inserting or reinserting lenses.

If the lens sticks (stops moving), the patient should be instructed to remove the lens. A few drops of non-preserved sterile saline solution may be applied directly to the eye to assist with removal. If non-movement of the lens continues after a few minutes, the patient should immediately consult their Eye Care Professional.

Do not use contact lens cleaning and disinfectant solutions with ACUVUE® Theravision™ with Ketotifen.

2.2 Contact Lens Fitting Information

See the ACUVUE® Theravision™ with Ketotifen Fitting Instruction Guide for professional fitting instructions and information.

3 DOSAGE FORMS AND STRENGTHS

Daily disposable etafilcon A drug-eluting contact lens with ketotifen (19 mcg per lens).

4 CONTRAINDICATIONS

4.1 Ocular Hyperemia

ACUVUE® Theravision™ with Ketotifen is contraindicated in patients with ocular hyperemia and should not be inserted into red or irritated eye(s). Remove ACUVUE Theravision with Ketotifen immediately if eye(s) becomes red or irritated.

4.2 Corneal Hypoesthesia

ACUVUE Theravision with Ketotifen is contraindicated in patients with decreased corneal sensation.

4.3 Corneal Infections

ACUVUE Theravision with Ketotifen is contraindicated in patients with any corneal infection (bacterial, fungal, protozoal or viral).

5 WARNINGS AND PRECAUTIONS

5.1 Corneal Ulcers

ACUVUE Theravision with Ketotifen should not be inserted if the patient has corneal epithelial breakdown, corneal ulceration, dry eye disease, injury or abnormality that affects the eyelids or anterior segment of the eye. Contact lens wear may worsen these conditions and lead to sight threatening complications. If a patient experiences eye discomfort, excessive tearing, vision changes, or redness of the eye, the patient should be instructed to immediately remove the lenses, and promptly contact the Eye Care Professional.

Studies have shown that when daily wear users wear their lenses overnight, the risk of ulcerative keratitis is greater than among those who do not wear them overnight. Contact lens wearers who are smokers have a higher incidence of corneal ulcers than nonsmokers.

5.2 Contact Lens-Related Complications

ACUVUE Theravision with Ketotifen should not be used to treat or prevent lens-related symptoms including irritation, discomfort or redness. ACUVUE Theravision with Ketotifen insertion could result in serious injury if a patient is experiencing these symptoms. Patients should be cautioned that proper use and care of contact lenses and lens care products are essential for the safe use of these products. If patients experience symptoms of contact lens intolerance or keratitis, the lens(es) should be IMMEDIATELY REMOVED.

5.3 Chemical Exposures

If chemicals of any kind (household products, gardening solutions, laboratory chemicals, etc.) are splashed into the eyes, the patient should: FLUSH EYES IMMEDIATELY WITH WATER AND IMMEDIATELY CONTACT THE EYE CARE PROFESSIONAL OR VISIT A HOSPITAL EMERGENCY ROOM WITHOUT DELAY.

5.4 Acanthamoeba Keratitis

ACUVUE Theravision with Ketotifen should not be worn while swimming or in hot tubs. The lens should not be rinsed in water from the tap. Tap water contains many impurities that can contaminate or damage the lenses and may lead to eye infection or injury. Contact lens wear in these settings increases the risk of sight threatening eye infections from microorganisms.

5.5 Backup Spectacles

Eye Care Professionals should instruct the patient to always have a functional pair of spectacles with a current prescription available to use if the patient becomes unable to wear contact lenses, or in circumstances where contact lens wear is not advised.

5.6 Eye Protection

Patients should be advised to notify the employer of being a contact lens wearer. Some jobs may require the use of eye protection equipment or may require that the patient not wear contact lenses.

5.7 Concomitant Use of Eye Drops or Eye Medications

Eye Drops or Eye Medications containing benzalkonium chloride should not be used simultaneously with ACUVUE® Theravision™ with Ketotifen. Wait at least 10 minutes after eye drop application before inserting lenses.

6 ADVERSE REACTIONS

The following clinically significant adverse reactions are described elsewhere in the labeling:

- Ocular Hyperemia [see Contraindications (4.1)]
- Corneal Hypoesthesia [see Contraindications (4.2)]
- Corneal Infections [see Contraindications (4.3)]
- Corneal Ulcers [see Warnings and Precautions (5.1)]
- Contact Lens-Related Complications [see Warning and Precautions (5.2)]
- Chemical Exposure [see Warnings and Precautions (5.3)]
- Acanthamoeba Keratitis [see Warnings and Precautions (5.4)]

6.1 Clinical Trials Experience

Because clinical trials are conducted under widely varying conditions, adverse reaction rates observed in the clinical trials of a product cannot be directly compared to rates in the clinical trials of another product and may not reflect the rates observed in practice.

The most commonly observed adverse reactions in clinical studies, occurring in ≥1% of ACUVUE® Theravision™ with Ketotifen treated eyes, were eye irritation, eye pain, and instillation site irritation.

8 USE IN SPECIFIC POPULATIONS

8.1 Pregnancy

Risk Summary

There are no adequate and well-controlled studies of ACUVUE® Theravison™ with Ketotifen administration in pregnant women to inform a drug-associated risk. ACUVUE® Theravison™ with Ketotifen is not absorbed systemically following ocular administration, and maternal use is not expected to result in fetal exposure to the drug. Oral administration of ketotifen fumarate to pregnant rats or rabbits did not produce teratogenicity at clinically relevant doses [see Data].

Data

Human Data

There are no human data that establish the presence or absence of drug-associated risk with the use of ACUVUE® Theravision™ with Ketotifen by pregnant women.

Animal Data

Oral administration of 45 mg/kg/day ketotifen to pregnant rabbits resulted in an increased incidence of retarded ossification of the sternebrae. This dose (normalized to body surface area) was approximately 23,000 times higher than the daily maximum recommended human ophthalmic dose (MRHOD) of 0.038 mg.

No adverse embryofetal effects were observed in rats or rabbits orally administered 100 mg/kg/day and 15 mg/kg/day, respectively, during organogenesis. These doses (normalized to body surface area) were approximately 26,000 and 7,700 times higher than the MRHOD, respectively.

An oral dose of 50 mg/kg/day ketotifen (approximately 13,000 times higher than MRHOD) administered to rats from Day 15 of pregnancy until Day 21 postpartum produced maternal toxicity, a slight increase in postnatal mortality and a slight decrease in body weight gain in offspring during the first four days post-partum.

8.2 Lactation

Risk Summary

There is no information regarding the presence or absence of ketotifen fumarate or its metabolites in human milk following use of ACUVUE® Theravision™ with Ketotifen, or on the breastfed infants and milk production. Ketotifen fumarate has been identified in breast milk in rats following oral administration. It is not known whether topical ocular administration could result in sufficient systemic absorption to produce detectable quantities in breast milk.

The development and health benefits of breastfeeding should be considered along with the mother's clinical need for ACUVUE® Theravision™ with Ketotifen and any potential adverse effects on the breast-fed child from ketotifen fumarate.

8.3 Pediatric Use

The safety and efficacy of ACUVUE® Theravision™ with Ketotifen in pediatric patients below the age of 11 years has not been established.

8.4 Geriatric Use

Clinical studies of etafilcon A with ketotifen did not include sufficient numbers of subjects aged 65 and over to determine whether they respond differently from younger subjects.

11 DESCRIPTION

ACUVUE® Theravision™ with Ketotifen is a sterile, soft (hydrophilic), spherical daily wear, daily disposable etafilcon A drug-eluting contact lens containing ketotifen, an H1 receptor antagonist, for topical administration to the eyes.

Ketotifen fumarate is a white to brownish-yellow, fine crystalline powder. The buffered packaging solution of ACUVUE® Theravision™ with Ketotifen has a pH range of 6.6 to 7.3 and an osmolality of not more than 460 mOsm/Kg. This product does not contain an antimicrobial preservative.

Contains:

Active: ketotifen 19 mcg equivalent to 43 mcg ketotifen fumarate per lens

Inactives: boric acid, calcium hydroxide, pentetic acid, sodium chloride, sodium borate, and water.

Chemical Name: 4,9-Dihydro-4-(1-methyl-4-piperidylidene)-10H-benzo[4,5]cyclohepta[1,2-b] thiophen-10-one fumarate (1:1).

Structural Formula:

Molecular formula of C19H19NOS∙C4H4O4 (C19H19NOS as free base)

Molecular weight of 425.50 g/mol (309.43 g/mol as the free base)

The contact lens material (etafilcon A) is a copolymer of 2-hydroxyethyl methacrylate and methacrylic acid cross-linked with 1, 1, 1-trimethylol propane trimethacrylate and ethylene glycol dimethacrylate. ACUVUE® Theravision™ with Ketotifen contact lenses are tinted blue using blue 2-hydroxyethyl methacrylate to make the lenses more visible for handling.

Physical/Optical Properties of the Lens:

Refractive Index: | 1.40
Visible Light Transmission: | 90% minimum
Ultraviolet Light Tranmission: (316 nm to 380 nm) UVA | 30% maximum
Ultraviolet Light Tranmission: (280 nm to 315 nm) UVB | 5% maximum
Surface Character: | Hydrophilic
Water Content: | 59%
Oxygen Permeability: | 21.4 × 10^-11(cm^2/sec) (mL O2/mL × mmHg) at 35°C (boundary corrected, edge corrected)

Dimensional Properties of the Lens:

Diameter: | 14.2 mm
Center Thickness: | Minus Lens - varies with power (e.g. -4.00D: 0.084 mm)
 | Plus Lens - varies with power (e.g. +4.00D: 0.190 mm)
Base Curve: | 8.5 mm and 9.0 mm
Power: | -0.50D to -10.00D (in 0.25D increments)
 | -10.50D to -12.00D (in 0.50D increments)
 | +0.50D to +6.00D (in 0.25D increments)

12 CLINICAL PHARMACOLOGY

12.1 Mechanism of Action

Device Component

In its hydrated state, the lens when placed on the cornea, acts as a refracting medium to focus light rays on the retina to correct refractive ametropia for as long as the lens is worn (up to 24 hours while awake).

Drug Component

Ketotifen fumarate, a benzocycloheptathiophene derivative, is a H1 receptor antagonist that stabilizes mast cells and prevents eosinophil accumulation. This action prevents the onset of ocular allergic itch allowing for continued lens wear during episodes of allergen exposure and has been demonstrated to last through 12 hours.

13 NONCLINICAL TOXICOLOGY

13.1 Carcinogenesis, Mutagenesis, Impairment of Fertility

Carcinogenesis

No information is available on the carcinogenic potential of ketotifen fumarate.

Mutagenesis

Ketotifen fumarate was determined to be non-mutagenic in a battery of in vitro and in vivo mutagenicity assays including: Ames test, in vitro chromosomal aberration test with V79 Chinese hamster cells, in vivo micronucleus assay in mouse, and mouse dominant lethal test. In addition, extracts of etafilcon A with ketotifen (19 mcg/lens) prepared in 0.9% sodium chloride or dimethyl sulfoxide were shown to be non-mutagenic in the Ames test.

Impairment of Fertility

Treatment of male rats with oral doses of ketotifen >10 mg/kg/day (approximately 2,600 times the MRHOD) for 70 days prior to mating resulted in mortality and a decrease in fertility. Treatment with ketotifen did not impair fertility in female rats receiving up to 50 mg/kg/day of ketotifen orally (approximately 13,000 times the MRHOD) for 15 days prior to mating.

14 CLINICAL STUDIES

The safety and efficacy of ACUVUE® Theravision™ with Ketotifen was assessed in two double-masked, randomized, placebo-controlled clinical conjunctival allergen challenge (CAC) studies (CR-4483 and CR-4484) and two 12-week safety studies (CR-4490 and CR-4539). Patients in these studies had allergic conjunctivitis induced by an ocular allergen challenge and refractive ametropia (myopia and hyperopia) suitable for contact lens wear without more than 1.00 D of astigmatism. A total of 244 patients (488 eyes) were evaluate in the CAC studies. A total of 491 subjects were exposed to ACUVUE® Theravision™ with Ketotifen over a period of 12 weeks in the safety studies. These four studies demonstrated that ACUVUE® Theravision™ with Ketotifen was safe and more effective than placebo (1•DAY ACUVUE®) in preventing ocular itching in patients with allergic conjunctivitis. ACUVUE® Theravision™ with Ketotifen reduced ocular itching within 3 minutes and the response was sustained for up to 12 hours after lens insertion. Visual acuity was comparable between ACUVUE® Theravision™ with Ketotifen and 1•DAY ACUVUE®.

Not all refractive powers, design configurations, or lens parameters available were tested in clinical investigation of the lenses. Therefore, when selecting an appropriate lens design, the Eye Care Professional should consider all characteristics of the lens that can affect lens performance and ocular health, including oxygen permeability, wettability, central and peripheral thickness and optic zone diameter. The potential impact of these factors on the patient's ocular health should be carefully weighed against the patient's need for refractive correction and prevention of itching associated with allergic conjunctivitis; therefore, the continuing ocular health of the patient and lens performance on the eye should be carefully monitored by the prescribing Eye Care Professional.

16 HOW SUPPLIED/STORAGE AND HANDLING

ACUVUE® Theravision™ with Ketotifen (etafilcon A drug-eluting contact lens with ketotifen) is a daily disposable contact lens, 19 mcg ketotifen per lens is supplied in a plastic blister bowl and a foil laminated lidstock containing a buffered ketotifen solution. The plastic package is marked with base curve, lens diameter, diopter (lens power), date of manufacture, expiration date and lot number.

ACUVUE® Theravision™ with Ketotifen is supplied in a 30-count carton containing 30 foil sealed blister packages containing etafilcon A contact lens with 19 mcg ketotifen (NDC 60123-019-30).

STORAGE AND HANDLING

Store at 15°C to 25°C (59°F to 77°F). Protect from light. Store lenses in carton until use.

DO NOT to use if the ACUVUE® Theravision™ with Ketotifen lens sterile blister package is opened or damaged.

17 PATIENT COUNSELING INFORMATION

Advise the patient to read the FDA-approved patient labeling (Patient Information).

Fitting

See the ACUVUE® Theravision™ with Ketotifen FITTING INSTRUCTION GUIDE for professional fitting instructions and information.

Wearing Schedule (Daily Wear)

Advise patients that ACUVUE® Theravision™ with Ketotifen should not be used to treat red eye(s). Remove lens(es) immediately if the eye(s) become red or irritated.

A single ACUVUE® Theravision™ with Ketotifen should be worn in each eye per day and should be discarded upon removal each day. The lens should not be worn beyond the period recommended by an eye care professional.

Advise patients that ACUVUE® Theravision™ with Ketotifen should be removed prior to sleep.

Lens Handling and Care

Advise patients to not use if the ACUVUE® Theravision™ with Ketotifen lens sterile blister package is opened or damaged.

Advise patients to always wash and rinse hands before handling lenses.

Advise patients to avoid contaminating hands or lenses with cosmetics, lotions, soaps, creams, deodorants or sprays. Instruct patients to put in lenses prior to applying makeup.

Advise patients not to touch contact lenses if hands have any foreign materials as microscopic scratches of the lenses may occur, which can cause distorted vision and/or injury to the eye.

Instruct patients to examine the lens after opening to be sure that it is a single, moist, clean lens that is free of any nicks or tears. If the lens appears damaged, patients should be instructed NOT to use it.

Instruct patients not to use contact lens cleaning and disinfectant solutions with ACUVUE® Theravision™ with Ketotifen. Discard lens after a single day's use.

Advise patients that ACUVUE® Theravision™ with Ketotifen should not be worn while swimming or in hot tubs. Contact lens wear in these settings increases the risk of sight threatening eye infections from microorganisms.

If the lens sticks (stops moving), the patient should be instructed to remove the lens. A few drops of non-preserved sterile saline solution may be applied directly to the eye to assist with removal. If non-movement of the lens continues after a few minutes, the patient should immediately consult their Eye Care Professional.

Patients should be advised to notify the employer of being a contact lens wearer. Some jobs may require the use of eye protection equipment or may require that the patient not wear contact lenses.

Advise patients to avoid all harmful or irritating vapors and fumes while wearing lenses. If aerosol products, such as hair spray, are used while wearing lenses, exercise caution and keep eyes closed until the spray has settled.

Instruct patients to never use tweezers, fingernails, or other tools to remove lenses from the lens container. Instead, patients should remove ACUVUE® Theravision™ with Ketotifen from the blister container packing solution using their fingertips. Patients should not touch the lens with fingernails.

The patients should be advised to never rinse the lenses in water from the tap. Tap water contains many impurities that can contaminate or damage the lenses and may lead to eye infection or injury.

Advise patients to always dispose of lenses when removed and have spare non-medicated lenses or spectacles available.

Concomitant Use of Other Medications

Advise patients to consult with their eyecare professional before using any medicine in the eyes. Advise patients that eye drops containing benzalkonium chloride should not be used simultaneously with ACUVUE® Theravision™ with Ketotifen. Instruct patients to wait 10 minutes after eye drop application before inserting lenses.

Daily self-examination

Instruct the patient to immediately remove the lens if any eye discomfort, eye pain, eye redness or decreased vision are experienced. If the symptoms stop after lens removal, the patient should discard the lens(es) and replace with new non-medicated lens(es). ACUVUE® Theravision™ with Ketotifen should not be worn for the remainder of the day. If the problem continue after inserting a new non-medicated lens, the patient should remove the lens and IMMEDIATELY CONSULT THEIR EYE CARE PROFESSIONAL.

Emergencies

Advise the patient that if chemicals of any kind (household products, gardening solutions, laboratory chemicals, etc.) are splashed into the eyes, the patient should: FLUSH EYES IMMEDIATELY WITH TAP WATER AND IMMEDIATELY CONTACT THE EYE CARE PROFESSIONAL OR VISIT A HOSPITAL EMERGENCY ROOM WITHOUT DELAY.

Symbols Key

The following symbols may appear on the label or packaging:

SYMBOL

DEFINITION

Caution, Consult Instructions for Use

Manufacturer

Date of Manufacture

Use by Date (expiration date)

Batch Code

Sterilized Using Steam Heat

Do Not Re-Use (Single Use)

Do Not Use if Package is Damaged

Store Away from Direct Sunlight

Indicates a Single Sterile Barrier System

Authorized Representative in the European Community

Medical Device in the European Community

Fee Paid for Waste Management

CE-mark and Identification Number of Notified Body

Contains Hazardous Substances

Contains a Medicinal Substance

CAUTION: U.S. Federal law restricts this device to sale by or on the order of a licensed practitioner

CONTACT LENS

Contact Lens

Lens Orientation Correct

Lens Orientation Incorrect (Lens Inside Out)

Package Opening Icon (Blister)

DIA

Diameter

BC

Base Curve

D

Diopter (Lens Power)

Distributed by:
Johnson & Johnson Vision Care, Inc.
7500 Centurion Parkway
Jacksonville, Florida 32256, USA
www.acuvue.com

©Johnson & Johnson Vision Care, Inc. 2021
In Canada: Johnson & Johnson Vision Care, division of Johnson & Johnson, Inc.
In USA: Johnson & Johnson Vision Care, Inc.
Printed in USA

Revision date: 2/2022
Revision number: XXXXX
ACUVUE® Theravision™ is a trademark of Johnson & Johnson Vision Care, Inc.

INSTRUCTIONS FOR USE

ACUVUE®
Theravision™ with Ketotifen
(etafilcon A lens with ketotifen)

For Eye Itch

for Daily Disposable Wear

FITTING INSTRUCTION GUIDE

Rx Only

CAUTION: US Federal law restricts this device to sale by or on the order of a licensed practitioner

PRODUCT DESCRIPTION

For full prescribing information see the ACUVUE® Theravision™ with Ketotifen Package Insert.

ACUVUE® Theravision™ with Ketotifen is a sterile, soft (hydrophilic), spherical etafilcon A drug-eluting contact lens containing ketotifen, an H1 receptor antagonist, for topical administration to the eyes.

Ketotifen fumarate is a white to brownish-yellow, fine crystalline powder with a molecular formula of C19H19NOS-C4H4O4 and formula weight of 425.50 g/mol. The buffered packaging solution of ACUVUE® Theravision™ with Ketotifen has a pH of 6.6 to 7.3 and an osmolality of 380 to 460 mOsm/Kg.

Contains:

Active: ketotifen 19 mcg per lens
Inactives: boric acid, calcium hydroxide, pentetic acid, sodium chloride, sodium borate, and water.

Chemical Name: 10H-Benzo[4,5]cyclohepta[1,2-b]thiophen-10-one, 4,9 dihydro-4-(1-methyl-4-piperidinylidene)-, hydrogen fumarate.

Structural Formula:

.This product does not contain an antimicrobial preservative.

The contact lens material (etafilcon A) is a copolymer of 2-hydroxyethyl methacrylate and methacrylic acid cross-linked with 1, 1, 1-trimethylol propane trimethacrylate and ethylene glycol dimethacrylate.

ACUVUE® Theravision™ with Ketotifen contact lenses are tinted blue using blue 2-hydroxyethyl methacrylate to make the lenses more visible for handling.

Physical/Optical Properties of the Lens:

- Specific Gravity (calculated): | 0.98 – 1.12
- Refractive Index: | 1.40
- Visible Light Transmittance: | 90% minimum
- Surface Character: | Hydrophilic
- Water Content: | 59%
- Oxygen Permeability (D/k):
VALUE 21.4 × 10^-11 (cm^2/sec) Fatt(boundary corrected, edge corrected) (ml O2/ml × mm Hg) at 35°C | METHOD

Dosage Forms and Strengths:

etafilcon A drug-eluting contact lens with ketotifen

(19 mcgper lens).

How Supplied:

Each ACUVUE® Theravision™ with Ketotifen (etafilcon A drug-eluting contact lens with ketotifen) lens is supplied in a foil-sealed plastic package containing a buffered ketotifen solution. The plastic package is marked with base curve, diopter power, diameter, lot number and expiration date.

AVAILABLE LENS PARAMETERS

The ACUVUE® Theravision™ with Ketotifen Brand Contact Lenses are hemispherical shells of the following dimensions:

Diameter (DIA): | 14.2 mm
Center Thickness: | Minus Lens - varies with power (e.g. -4.00D: 0.084 mm) Plus Lens - varies with power (e.g. +4.00D: 0.190 mm)
Base Curve (BC): | 8.5 mm and 9.0 mm
Powers (D): | -0.50D to -10.00D (in 0.25D increments) -10.50D to -12.00D (in 0.50D increments) +0.50D to +6.00D (in 0.25D increments)

ACTIONS

See CLINICAL PHARMACOLOGY, Mechanism of Action section of the ACUVUE® Theravision™ with Ketotifen Package Insert.

INDICATIONS AND USES

See INDICATIONS AND USAGE section of the ACUVUE® Theravision™ with Ketotifen Package Insert.

CONTRAINDICATIONS (REASONS NOT TO USE)

See CONTRAINDICATIONS section of the ACUVUE® Theravision™ with Ketotifen Package Insert.

WARNINGS

See WARNINGS AND PRECAUTIONS section of the ACUVUE® Theravision™ with Ketotifen Package Insert.

PRECAUTIONS

See WARNINGS AND PRECAUTIONS section of the ACUVUE® Theravision™ with Ketotifen Package Insert.

ADVERSE REACTIONS

See ADVERSE REACTIONS section of the ACUVUE® Theravision™ with Ketotifen Package Insert.

FITTING

GENERAL FITTING GUIDELINES

Patient Selection

You should first assess the patient's needs to ensure that the patient is an appropriate candidate for ACUVUE® Theravision™ with Ketotifen. ACUVUE® Theravision™ with Ketotifen, like other soft contact lenses, will require the appropriate and usual physiological and diagnostic assessments necessary to ensure proper patient selection.

Pre-Fitting Examination

A pre-fitting patient history and examination are necessary to:

- Determine whether a patient is a suitable candidate for ACUVUE® Theravision™ with Ketotifen Contact Lens (consider allergies, patient hygiene and mental and physical state), and
- Take ocular measurements for the initial contact lens parameter selection, and
- Collect and record baseline clinical information to which post-fitting examination results can be compared.

A pre-fitting examination may include a determination of optimal distance and near spectacle correction and corneal curvature measurements. The near correction should be determined at the midpoint of the patient's habitual reading distance. When more than one power provides optimal reading performance, prescribe the least plus (most minus) of the powers that meet the patient's requirements.

Lens Selection

A. Initial Power Determination

A spectacle refraction should be performed to establish the patient's baseline refractive status and to guide in the selection of the appropriate lens power. Remember to compensate for vertex distance if the refraction is greater than ±4.00 D.

B. Base Curve Selection (Trial Lens Fitting)

An 8.5mm/14.2mm ACUVUE® Theravision™ with Ketotifen Contact Lens should be the initial lens of choice for myopic patients regardless of keratometry readings. However, corneal curvature measurements should be performed to establish the patient's baseline ocular status.

An 8.5mm/14.2mm ACUVUE® Theravision™ with Ketotifen Contact Lens should be placed on each of the patient's eyes and evaluated after the patient has adjusted to the lenses. A properly fit lens will center and completely cover the cornea (i.e., no limbal exposure), have sufficient movement with the blink to provide tear exchange under the contact lens and be comfortable. The lens should move freely when manipulated digitally with the lower lid, and then return to its properly centered position when released. If resistance is encountered when pushing the lens up, the lens is fitting tightly and should not be dispensed to the patient.

A steep fitting lens may exhibit one or more of the following characteristics: insufficient movement with the blink, conjunctival indentation and resistance when pushing the lens up digitally with the lower lid. If the 8.5mm/14.2mm ACUVUE® Theravision™ with Ketotifen Contact Lens is judged to be steep fitting, it should not be dispensed to the patient.

A flat fitting lens may exhibit one or more of the following characteristics: decentration, incomplete corneal coverage (i.e., limbal exposure), excessive movement with the blink or edge standoff. If the 8.5mm/14.2mm ACUVUE® Theravision™ with Ketotifen Contact Lens is judged to be flat fitting, it should not be dispensed to the patient.

If the initial ACUVUE® Theravision™ with Ketotifen Contact Lens base curve is judged to be flat or steep fitting, the alternate base curve, if available, should be considered.

C. Final Lens Power

A spherical over-refraction should be performed to determine the final lens power after the lens fit is judged acceptable. The spherical over-refraction should be combined with the trial lens power to determine the final lens prescription.

Example 1:
  Diagnostic lens: -2.00 D
    Spherical over-refraction -0.25 D
    Final lens power: -2.25 D
Example 2:
  Diagnostic lens: -2.00 D
    Spherical over-refraction +0.25 D
    Final lens power: -1.75 D

MONOVISION FITTING GUIDELINES

Patient Selection

A. Monovision Needs Assessment

For a good prognosis the patient should have adequately corrected distance and near visual acuity in each eye. The amblyopic patient or the patient with significant astigmatism (greater than 1.00D) in one eye may not be a good candidate for monovision correction with the ACUVUE® Theravision™ with Ketotifen Contact Lens.

Occupational and environmental visual demands should be considered. If the patient requires critical vision (visual acuity and stereopsis), it should be determined by trial whether this patient can function adequately with monovision correction.

Monovision contact lens wear may not be optimal for such activities as:

(1) Visually demanding situations such as operating potentially dangerous machinery or performing other potentially hazardous activities: and
(2) Driving automobiles (e.g., driving at night). Patients who cannot pass their state drivers license requirements with monovision correction should be advised to not drive with this correction, OR may require that additional over-correction be prescribed

B. Patient Education

All patients do not function equally well with monovision correction. Patients may not perform as well for certain tasks with this correction as they have with bifocal reading glasses. Each patient should understand that monovision, as well as other presbyopic alternatives, can create a vision compromise that may reduce visual acuity and depth perception for distance and near tasks. During the fitting process it is necessary for the patient to realize the disadvantages as well as the advantages of clear near vision and straight ahead and upward gaze that monovision contact lenses provide.

Eye Selection

Generally, the non-dominant eye is corrected for near vision. The following two methods for eye dominance can be used.

A. Ocular Preference Determination Methods

Method 1 Determine which eye is the "sighting eye". Have the patient point to an object at the far end of the room. Cover one eye. If the patient is still pointing directly at the object, the eye being used is the dominant (sighting) eye.
Method 2 Determine which eye will accept the added power with the least reduction in vision. Place a hand-held trial lens equal to the spectacle near ADD in front of one eye and then the other while the distance refractive error correction is in place for both eyes. Determine whether the patient functions best with the near ADD lens over the right or left eye.

Other methods include the refractive error method and the visual demands method.

B. Refractive Error Method

For anisometropic correction, it is generally best to fit the more hyperopic (less myopic) eye for distance and the more myopic (less hyperopic) eye for near.

C. Visual Demands Method

Consider the patient's occupation during the eye selection process to determine the critical vision requirements. If a patient's gaze for near tasks is usually in one direction, correct the eye on that side for near.

Example:
A writer who places copy to the left side of the desk will function best with the near lens on the left eye.

SPECIAL FITTING CHARACTERISTICS

Near ADD Determination

Always prescribe the lens power for the near eye that provides optimal near acuity at the midpoint of the patient's habitual reading distance. However, when more than one power provides optimal reading performance, prescribe the least plus (most minus) of the powers.

Trial Lens Fitting

A trial fitting is performed in the office to allow the patient to experience monovision correction. Lenses are fit according to the General Fitting Guidelines for base curve selection described in this guide.

Case history and standard clinical evaluation procedure should be used to determine the prognosis. Determine the distance correction and the near correction. Next determine the near ADD. With trial lenses of the proper power in place, observe the reaction to this mode of correction.

Allow the lenses to settle for about 20 minutes with the correct power lenses in place. Walk across the room and have the patient look at you. Assess the patient's reaction to distance vision under these circumstances. Then have the patient look at familiar near objects such as a watch face or fingernails. Again assess the reaction. As the patient continues to look around the room at both near and distance objects, observe the reactions. Only after these vision tests are completed should the patient be asked to read print. Evaluate the patient's reaction to large print (e.g., typewritten copy) at first and then graduate to newsprint and finally smaller type sizes.

After the patient's performance, under the above conditions, is completed, tests of visual acuity and reading ability under conditions of moderately dim illumination should be attempted.

An initial unfavorable response in the office, while indicative of a guarded prognosis, should not immediately rule out a more extensive trial under the usual conditions in which a patient functions.

Adaptation

Visually demanding situations should be avoided during the initial wearing period. A patient may at first experience some mild blurred vision, dizziness, headaches and a feeling of slight imbalance. You should explain the adaptational symptoms to the patient. These symptoms may last for a brief minute or for several weeks. The longer these symptoms persist, the poorer the prognosis for successful adaptation.

To help in the adaptation process, the patient can be advised to first use the lenses in a comfortable familiar environment such as in the home.

Some patients feel that automobile driving performances may not be optimal during the adaptation process. This is particularly true when driving at night. Before driving a motor vehicle, it may be recommended that the patient be a passenger first to make sure that their vision is satisfactory for operating an automobile. During the first several weeks of wear (when adaptation is occurring), it may be advisable for the patient to only drive during optimal driving conditions. After adaptation and success with these activities, the patient should be able to drive under other conditions with caution.

Other Suggestions

The success of the monovision technique may be further improved by having your patient follow the suggestions below. Remember to advise patients to use only one ACUVUE® Theravision™ with Ketotifen Contact Lens per eye per day.

- Have a third contact lens (distance power) to use when critical distance viewing is needed.
- Have a third contact lens (near power) to use when critical near viewing is needed.
- Having supplemental spectacles to wear over the monovision contact lenses for specific visual tasks may improve the success of monovision correction. This is particularly applicable for those patients who cannot meet state driver licensing requirements with a monovision correction.
- Make use of proper illumination when carrying out visual tasks.

Success in fitting monovision can be improved by the following suggestions:

- Reverse the distance and near eyes if a patient is having trouble adapting.
- Refine the lens powers if there is trouble with adaptation. Accurate lens power is critical for presbyopic patients.
- Emphasize the benefits of clear near vision and straight ahead and upward gaze with monovision.

The decision to fit a patient with a monovision correction is most appropriately left to the Eye Care Professional in conjunction with the patient after carefully considering the patient's needs.

PATIENT COUNSELING INFORMATION (PATIENT MANAGEMENT)

Dispensing Visit

- Evaluate the physical fit and visual acuity of the lens on each eye.
- Teach the patient how to insert and remove his or her lenses.
- Explain the daily wear regimen and schedule a follow-up examination.

Provide the patient with a copy of the ACUVUE® Theravision™ with Ketotifen patient instructions. Review these instructions with the patient so that he or she clearly understands the prescribed wearing and replacement schedule.

Review with the patient that no cleaning or disinfection is needed with daily disposable lenses. Patients should always dispose of lenses when they are removed and have spectacles or non-medicated lenses available.

Follow-Up Examinations

Follow-up care (necessary to ensure continued successful contact lens wear) should include routine periodic progress examinations, management of specific problems, if any, and a review with the patient of the wear schedule, lens replacement schedule, and proper lens care and handling procedures.

Recommended Follow-up Examination Schedule for ACUVUE® Theravision™ with Ketotifen for Daily Disposable Wear: (complications and specific problems should be managed on an individual patient basis):

- One week from the initial lens dispensing to patient.
- One month post-dispensing.
- Every three to six months thereafter.

NOTE: Preferably, at the follow-up visits, lenses should be worn for at least six hours.

Recommended Procedures for Follow-Up Visits:

- Solicit and record patient's symptoms, if any.
- Measure visual acuity monocularly and binocularly at distance and near with the contact lenses.
- Perform an over-refraction at distance and near to check for residual refractive error.
- With the biomicroscope, judge the lens fitting characteristics (as described in the "General Fitting Guidelines") and evaluate the lens surface for deposits and damage.
- Following lens removal, examine the cornea and conjunctiva with the biomicroscope and fluorescein.
  - The presence of vertical corneal striae in the posterior central cornea and/or corneal neovascularization is indicative of excessive corneal edema.
  - The presence of corneal staining and/or limbal-conjunctival hyperemia can be indicative of an unclean lens, a reaction to solution preservatives, excessive lens wear and/or a poorly fitting lens.
  - Papillary conjunctival changes may be indicative of an unclean and/or damaged lens.
- Periodically perform keratometry and spectacle refractions. The values should be recorded and compared to the baseline measurements.

If any observations are abnormal, use professional judgment to alleviate the problem and restore the eye to optimal conditions. If the criteria for successful fit are not satisfied during any follow-up examinations, repeat the patient's trial fitting procedure and refit the patient.

WEARING SCHEDULE (DAILY WEAR)

DOSAGE AND ADMINISTRATION

- Insert one lens per eye per day. Discard lens after a single day's use.
- If prevention or relief of itching is needed beyond twelve hours, remove ACUVUE® Theravision™ with Ketotifen and consult your eye care professional.
- ACUVUE® Theravision™ with Ketotifen may be worn beyond twelve hours for vision correction. Lenses should be removed prior to sleeping.

ADDITIONAL INFORMATION

- The maximum daily wearing time should be determined by the Eye Care Professional based upon the patient's individual response to contact lenses. Regular checkups, as determined by the Eye Care Professional, are also extremely important.
- Patients tend to over wear the lenses initially. The Eye Care Professional should emphasize the importance of adhering to the initial maximum daily wearing time. Maximum wearing time should be determined by the Eye Care Professional based upon the patient's physiological eye condition, because individual response to contact lenses varies.
- ACUVUE® Theravision™ with Ketotifen is intended to be worn once on a daily disposable basis (less than 24 hours, while awake) and should be discarded upon removal. Studies have not been performed to show that ACUVUE® Theravision™ with Ketotifen is safe to wear during sleep.
- Patients should never wear lenses beyond the period recommended by the Eye Care Professional.

REPLACEMENT SCHEDULE

- These lenses are indicated for disposable wear and should be discarded upon removal.

LENS CARE DIRECTIONS

For Lenses Prescribed for Single Use Disposable Wear:

- The Eye Care Professional should review with patients that no cleaning or disinfection is needed with disposable lenses. Patients should always dispose of lenses when they are removed and have replacement non-medicated lenses or spectacles available.

Care for Sticking (Non-Moving) Lenses

- During removal, if the lens sticks to the eye, the patient should be instructed to apply a few drops of non-preserved sterile saline solution directly to the eye and wait until the lens begins to move freely on the eye before removing it. If non-movement of the lens continues after a few minutes, the patient should immediately contact the Eye Care Professional.

STORAGE CONDITIONS

Store at 15°C to 25°C (59°F to 77°F); with excursions permitted up to 30°C (86°F).

Protect from light. Store lenses in carton until use.

EMERGENCIES

The patient should be informed that if chemicals of any kind (household products, gardening solutions, laboratory chemicals, etc.) are splashed into the eyes, the patient should: FLUSH EYES IMMEDIATELY WITH TAP WATER AND IMMEDIATELY CONTACT THE EYE CARE PROFESSIONAL OR VISIT A HOSPITAL EMERGENCY ROOM WITHOUT DELAY.

REPORTING OF ADVERSE REACTIONS

All serious adverse experiences and adverse reactions observed in patients wearing these lenses or experienced with the lenses should be reported to:

Johnson & Johnson Vision Care, Inc.
7500 Centurion Parkway
Jacksonville, Florida 32256, USA
www.acuvue.com

©Johnson & Johnson Vision Care, Inc. 2021
In Canada: Johnson & Johnson Vision Care, division of Johnson & Johnson, Inc.
In USA: Johnson & Johnson Vision Care, Inc.
Printed in USA
Revision date: 2/2022
Revision number: XXXXXX
ACUVUE® Theravision™ is a trademark of Johnson & Johnson Vision Care, Inc.

INSTRUCTIONS FOR USE

ACUVUE®
Theravision™ with Ketotifen
(etafilcon A drug-eluting contact lens with ketotifen)

Contact lenses for daily wear (1-Day)

Contents: 30 etafilcon A drug-eluting contact lenses (59% H2O) in a buffered ketotifen solution. Each lens contains 19 mcg ketotifen.

PATIENT INSTRUCTION GUIDE

Rx Only

CAUTION: US Federal law restricts this device to sale by or on the order of a licensed practitioner

Dosage: See prescribing information

Light sensitive. Store blister packages in the carton until use

USA= Johnson & Johnson Vision Care, Inc., Jacksonville, FL 32256, USA
IRELAND= Johnson & Johnson Vision Care Ireland UC, Limerick, Ireland
© 2021 Johnson & Johnson Vision Care Companies
www.acuvue.com

SYMBOLS KEY

The following symbols may appear on the label or packaging:

SYMBOL

DEFINITION

Caution, Consult Instructions for Use

Manufacturer

Date of Manufacture

Use by Date (expiration date)

Batch Code

Sterilized Using Steam Heat

Do Not Re-Use (Single Use)

Do Not Use if Package is Damaged

Store Away from Direct Sunlight

Indicates a Single Sterile Barrier System

Authorized Representative in the European Community

Medical Device in the European Community

Fee Paid for Waste Management

CE-mark and Identification Number of Notified Body

Contains Hazardous Substances

Contains a Medicinal Substance

CAUTION: U.S. Federal law restricts this device to sale by or on the order of a licensed practitioner

CONTACT LENS

Contact Lens

Lens Orientation Correct

Lens Orientation Incorrect (Lens Inside Out)

Package Opening Icon (Blister)

DIA

Diameter

BC

Base Curve

D

Diopter (Lens Power)

INDICATIONS

ACUVUE® Theravision™ with Ketotifen are daily wear, daily disposable drug-eluting contact lenses containing an antihistamine to prevent ocular itch due to allergic conjunctivitis and correction of refractive ametropia (myopia and hyperopia) in patients who do not have red eye(s), are suitable for contact lens wear and do not have more than 1.00 D of astigmatism. Itchy eye prevention has been demonstrated to last up to 12 hours in clinical trials; however, the lens may be worn for longer than 12 hours for vision correction.

WEARING INSTRUCTIONS

DO NOT WEAR YOUR LENSES WHILE SLEEPING.

The ACUVUE® Theravision™ with Ketotifen described in this booklet are prescribed by your Eye Care Professional for daily disposable wear and are to be discarded after each removal. You should:

- Insert one lens per eye per day. Discard lens after a single day's use.
- If prevention or relief of itching is needed beyond twelve hours, consult your Eye Care Professional.
- These lenses may be worn beyond twelve hours for vision correction. Lenses should be removed prior to sleeping.
- Do not use contact lens cleaning and disinfectant solutions with ACUVUE® Theravision™ with Ketotifen.

WHEN LENSES SHOULD NOT BE WORN (CONTRAINDICATIONS)

DO NOT USE these lenses when you have any of the following conditions:

- Red or irritated eye(s). Remove contact lens(es) immediately if eye(s) become red while wearing;
- Inflammation or infection in or around the eye or eyelids
- Any eye disease, injury, or abnormality that affects the cornea, conjunctiva, or eyelids
- Any previously diagnosed condition that makes contact lens wear uncomfortable
- Severe dry eye
- Reduced corneal sensitivity
- Any medical condition that may affect the eye or be made worse by wearing contact lenses
- Allergic reactions on the surface of the eye or surrounding tissues that may be induced or made worse by wearing contact lenses
- Any active eye infection
- Known hypersensitivity to any ingredient in this product

WARNINGS

What You Should Know About Contact Lens Wear:

EYE PROBLEMS, INCLUDING CORNEAL ULCERS, CAN DEVELOP RAPIDLY AND LEAD TO LOSS OF VISION. IF YOU EXPERIENCE:

Eye Discomfort,
Excessive Tearing,
Vision Changes,
Loss of Vision,
Eye Redness, or
Other Eye Problems,

YOU SHOULD IMMEDIATELY REMOVE THE LENSES, AND PROMPTLY CONTACT YOUR EYE CARE PROFESSIONAL.

- These lenses should not be used to treat red eye(s). Remove lens(es) immediately if your eyes become red or irritated.
- Lenses prescribed for daily disposable wear (i.e., your Eye Care Professional instructs you to remove and discard your lenses at the end of each day), should not be worn while sleeping. Clinical studies have shown the risk of serious eye problems is increased when lenses are worn overnight.
- Contact lens wearers who are smokers have a higher incidence of corneal ulcers than nonsmokers.
- Problems with contact lenses or lens care products could result in serious injury to the eye.
- Proper use and care of your contact is essential for the safe use of these products.
- The overall risk of serious eye problems may be reduced by carefully following directions for lens care.

Specific Instructions for Use and Warnings:

Water Activity

Instruction for Use

Do not expose your contact lenses to water while you are wearing them.

WARNING:

Water can harbor microorganisms that can lead to severe infection, vision loss, or blindness. If your lenses have been submersed in water when participating in water sports or swimming in pools, hot tubs, lakes, or oceans, you should discard them and replace them with a new pair. Ask your Eye Care Professional for recommendations about wearing your lenses during any activity involving water.

PRECAUTIONS

For your eye health, it is important to carefully follow the handling, insertion, removal, and wearing instructions in this booklet, as well as those prescribed by your Eye Care Professional (see "Lens Handling & Insertion", "Lens Wearing" and "Caring for your Lenses" sections).

General Precautions:

Do Not use contact lens care solutions with this product

If you wear your contact lenses to correct presbyopia using monovision you may not be able to get the best corrected visual acuity for either far or near vision. Visual needs are different for different people, so your Eye Care Professional should work with you when selecting the most appropriate type of lens for you.

Always contact your Eye Care Professional before using any medicine in your eyes.

Be aware that certain medications, such as antihistamines, decongestants, diuretics, muscle relaxants, tranquilizers, oral contraceptives, and those for motion sickness may cause dryness of the eye, increased lens awareness (feeling of the lens in the eye), or blurred vision. Always inform your Eye Care Professional if you experience any problems with your lenses while taking such medications.

Do not change lens type (e.g. brand name, etc.) or parameters (e.g. diameter, base curve, lens power, etc.) without consulting your Eye Care Professional.

Consult your Eye Care Professional or Health Care Provider if you are pregnant or nursing a baby.

As with any contact lens, follow-up visits are necessary to assure the continuing health of your eyes. Ask your Eye Care Professional about the recommended follow-up schedule.

Who Should Know That You are Wearing Contact Lenses:

Inform all of your doctors (Health Care Professionals) about being a contact lens wearer.

Always inform your employer of being a contact lens wearer. Some jobs may require use of eye protection equipment or may require that you not wear contact lenses.

ADVERSE REACTIONS

(POSSIBLE PROBLEMS WITH LENS WEAR AND WHAT TO DO)

Possible Problems

The most commonly observed ocular adverse reactions in clinical studies, occurring in < 2% of treated eyes, were eye irritation, eye pain, and instillation site irritation.

Other potential lens related side effects are discussed in greater detail in other sections of this guide:

Risk of Developing Corneal Ulcers (See WARNINGS)

Other Contact Lens Related Problems

Be aware that problems can occur while wearing contact lenses and may be associated with the following symptoms:

- burning, stinging, itchy, and/or dry eyes
- reduced lens comfort
- feeling of something in your eye (foreign body, scratched area)
- swelling or inflammation in or around the eyes
- eye redness
- eyelid problems
- watery eyes and/or unusual eye secretion
- poor vision
- blurred vision
- rainbows or halos around objects
- sensitivity to light (photophobia)

When any of the above symptoms occur, a serious eye condition may be present. You should immediately be seen by your Eye Care Professional, so that the problem can be identified and treated, if necessary, in order to avoid serious eye damage.

This product should not be used to treat or prevent lens-related symptoms including irritation, discomfort, or redness.

Recognizing Problems and What To Do

You should conduct a simple 3-part self-examination at least once a day. Ask yourself:

- How do the lenses feel on my eyes?
- How do my eyes look?
- Have I noticed a change in my vision?

If you notice any problems, you should IMMEDIATELY REMOVE YOUR LENS AND CONTACT YOUR EYE CARE PROFESSIONAL.

LENS HANDLING AND INSERTION

For your eye health, it is important to carefully follow the handling, insertion, removal, and wearing instructions in this booklet, as well as those prescribed by your Eye Care Professional. If you will not or cannot always follow the recommended care procedures, you should not attempt to wear contact lenses.

When you first get your lenses, be sure that you are able to put the lenses on and remove them (or have someone else available who can remove the lenses for you) before leaving your Eye Care Professional's office.

Step 1: Getting Started

It is essential that you learn and use good hygiene in the care and handling of your new lenses.

Cleanliness is the first and most important aspect of proper contact lens care. In particular, your hands should be clean, dry, and free of any soaps, lotions, or creams before you handle your lenses.

Before you start:

Always wash your hands thoroughly with a mild soap, rinse completely, and dry with a lint-free towel before touching your lenses.

You should avoid the use of soaps containing cold cream, lotion, or cosmetics before handling your lenses. These substances may come into contact with the lenses and interfere with successful wearing. It is best to put on your lenses before putting on makeup

Step 2: Opening the Packaging

Multi-pack

Always confirm the lens parameters (e.g. diameter (DIA), base curve (BC), lens power (D), etc.) printed on the multi-pack and on the individual lens package match your prescription. DO NOT use if there is a mismatch.

Each multi-pack contains individually packaged lenses. Each lens comes in its own lens package designed specifically to keep it sterile while sealed.

These lenses are sensitive to light – store individual blister packages in the carton until use.

Lens Package

DO NOT use if the sterile blister package is opened or damaged.

To open an individual lens package, follow these simple steps:

1. Shake the lens package and check to see that the lens is floating in the solution.
2. Carefully peel back the foil closure to reveal the lens.
3. Place a finger on the lens and slide the lens up the side of the bowl of the lens package until it is free of the container.

Occasionally, a lens may stick to the inside surface of the foil when opened, or to the plastic package itself. This will not affect the sterility of the lens. It is still perfectly safe to use. Carefully remove and inspect the lens following the handling instructions.

NEVER use tweezers or other tools to remove your lenses from the lens container.

Lens Handling Tips

- Handle your lenses with your fingertips, and be careful to avoid contact with fingernails. It is helpful to keep your fingernails short and smooth.
- Develop the habit of always working with the same lens first to avoid mix-ups.
- After you have removed the lens from the packaging, examine it to be sure that it is a single, moist, clean lens that is free of any nicks or tears. If the lens appears damaged, DO NOT use it.

Step 3: Placing the Lens on the Eye

Remember, always start with the same eye.

Once you have opened the lens package, removed, and examined the lens, follow these steps to insert the lens into your eye:

1. BE SURE THE LENS IS NOT INSIDE-OUT by following one of the following procedures:
  - Place the lens on the tip of your index finger and check its profile. The lens should assume a natural, curved, bowl-like shape. If the lens edges tend to point outward, the lens is inside out.
  - Gently squeeze the lens between the thumb and forefinger. The edges should turn inward. If the lens is inside out, the edges will turn slightly outward.
    OR
  - Place the lens on the tip of your index finger and, looking up at the lens, locate the numbers 1-2-3. 1-2-3 indicates correct orientation, while a reverse of 1-2-3 indicates the lens is inside out. If the lens is inside out (reverse 1-2-3), invert the lens and locate the numbers again to confirm correct lens orientation.
2. With the lens on your index finger, use your other hand to hold your upper eyelid so you won't blink.
3. Pull down your lower eyelid with the other fingers of your "inserting" hand.
4. Look up at the ceiling and gently place the lens on the lower part of your eye.
5. Slowly release your eyelid and close your eye for a moment.
6. Blink several times to center the lens.
7. Use the same technique when inserting the lens for your other eye.

There are other methods of lens placement. If the above method is difficult for you, ask your Eye Care Professional for an alternate method.

Step 4: Checking Your Lenses

After you have successfully inserted your lenses, you should ask yourself:

- Do I see well?
- How do the lenses feel on my eyes?
- How do my eyes look?

If after placement of the lens, your vision is blurred, check for the following:

The lens is not centered on the eye (see "Step 5: Centering the Lens," next in this booklet).

If the lens is centered, remove the lens (see "Removing Your Lenses") and check for the following:

- Cosmetics or oils on the lens. Dispose of the lens and insert a new fresh lens.
- The lens is on the wrong eye.
- The lens is inside out (it would also not be as comfortable as normal). See "Step 3: Placing the Lens on the Eye."

If you find that your vision is still blurred after checking the above possibilities, remove the lens and consult your Eye Care Professional.

Note: If a lens is noticeably uncomfortable upon insertion or becomes less comfortable than when it was first inserted, remove the lens immediately and contact your Eye Care Professional. If your examination of your eyes and the lenses shows any other problems, IMMEDIATELY REMOVE YOUR LENSES AND CONTACT YOUR EYE CARE PROFESSIONAL.

Step 5: Centering the Lens

A lens, which is on the cornea (center of your eye), will very rarely move onto the white part of the eye during wear. This, however, can occur if insertion and removal procedures are not performed properly. To center a lens, follow either of these procedures:

- Close your eyelids and gently massage the lens into place through the closed lids.
  OR
- Gently move the off-centered lens onto the cornea (center of your eye) while the eye is opened using finger pressure on the edge of the upper lid or lower lid.

LENS WEARING

While wearing your lenses, remember the following important precautions:

Hazardous Conditions

If you use aerosol (spray) products, such as hair-spray, while wearing lenses, keep your eyes closed until the spray has settled.

Avoid all harmful or irritating vapors and fumes while wearing lenses.

Never rinse your lenses in water from the tap. Tap water contains many impurities that can contaminate or damage your lenses and may lead to eye infection or injury.

Water Activity

- Do not expose your contact lenses to water while you are wearing them.

Lubricating/Rewetting Solutions

Lubricating/Rewetting Solutions should not be used with these lenses. If the lens sticks (stops moving), a few drops of non-preserved sterile saline may be applied to assist with removal.

Do not use saliva or anything other than the recommended solutions for lubricating or rewetting your lenses. Do not put lenses in your mouth.

Sharing Lenses

Never allow anyone else to wear your lenses. Sharing lenses greatly increases the chance of eye infections.

Adhering to the Prescribed Wearing & Replacement Schedules

Never wear your lenses beyond the amount of time recommended by your Eye Care Professional. Never wear more than one lens per day.

Always throw away worn lenses as prescribed by your Eye Care Professional.

REMOVING YOUR LENSES

CAUTION: Always be sure the lens is on the cornea (center of your eye) before attempting to remove it. Determine this by covering the other eye. If vision is blurred, the lens is either on the white part of the eye or it is not on the eye at all. To locate the lens, inspect the upper area of the eye by looking down into a mirror while pulling the upper lid up. Then inspect the lower area by pulling the lower lid down.

1. Wash, rinse, and dry your hands thoroughly. You should follow the method that is recommended by your Eye Care Professional. Below is an example of one method: the Pinch Method.
  Pinch Method:
  Step 1. Look up, slide the lens to the lower part of the eye using the forefinger.
  Step 2. Gently pinch the lens between the thumb and forefinger.
  Step 3. Remove the lens.
2. Follow the instructions in the next section, "Caring for Your Lenses".

NOTE: For your eye health, it is important that the lens moves freely on your eye. If the lens sticks (stops moving) on your eye, apply a few drops of the recommended rewetting solution. Wait until the lens begins to move freely on the eye before removing it. If non-movement of the lens continues, you should immediately consult your Eye Care Professional.

CARING FOR YOUR LENSES

Remember, there is no cleaning or disinfection needed with these lenses. Always dispose of lenses when they are removed and have replacement non-medicated lenses or glasses available. Any unused product or waste material should be disposed of in accordance with local requirements.

Lens Storage:

- Store these lenses at room temperature
- These lenses are sensitive to light – store individual blister packages in the carton until use.

EMERGENCIES

If chemicals of any kind (household products, gardening solutions, laboratory chemicals, etc.) are splashed into your eyes: FLUSH EYES IMMEDIATELY WITH TAP WATER AND IMMEDIATELY CONTACT YOUR EYE CARE PROFESSIONAL OR VISIT A HOSPITAL EMERGENCY ROOM RIGHT AWAY.

INSTRUCTIONS FOR THE PRESBYOPIC PATIENT

The decision to be fit with monovision correction is most appropriately left to your Eye Care Professional, in conjunction with you, after carefully considering and discussing your needs.

Johnson & Johnson Vision Care, Inc.
7500 Centurion Parkway
Jacksonville, FL 32256
USA
Tel: 1-800-843-2020
www.acuvue.com

© Johnson & Johnson Vision Care, Inc. 2021
In Canada: Johnson & Johnson Vision Care division of Johnson & Johnson Inc.
In USA: Johnson & Johnson Vision Care, Inc

Revision Date: 2/2022
Revision number: XXXXX

PRINCIPAL DISPLAY PANEL - 30 Lens Blister Pack Carton

NDC 60123-019-30

19 mcg per lens

ACUVUE®
Theravision™ with Ketotifen
(etafilcon A drug-eluting contact lens with ketotifen)

1 DAY
FOR EYE ITCH
30 CONTACT LENSES